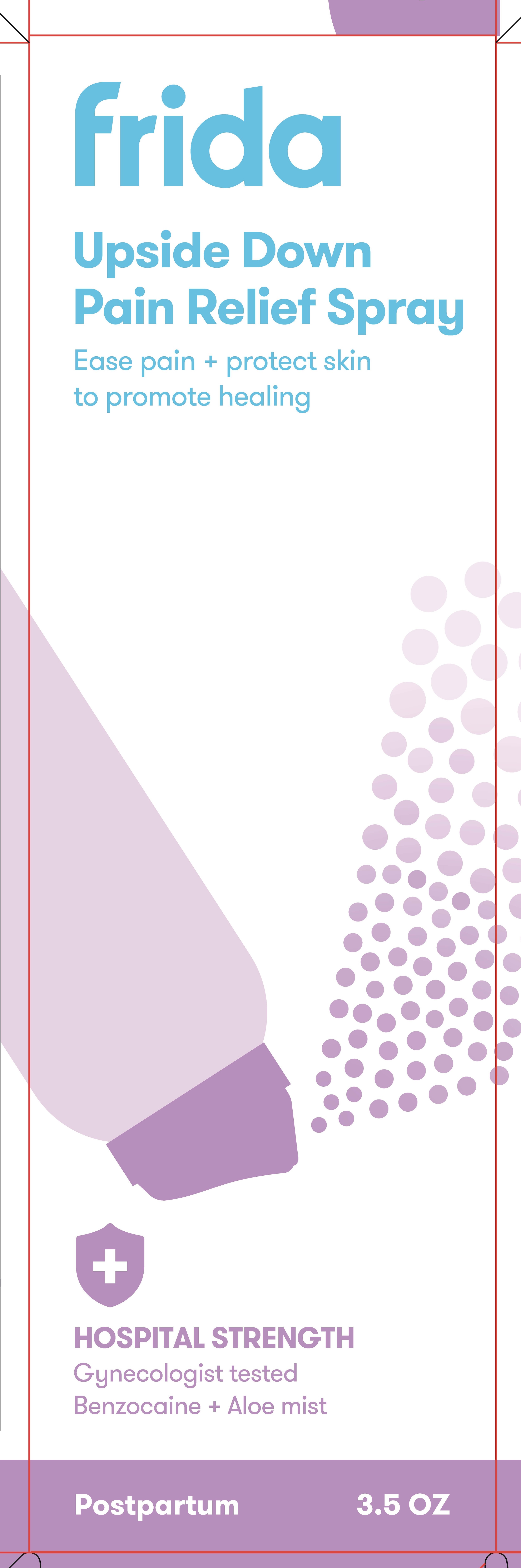 DRUG LABEL: Upside Down Pain Relief
NDC: 72705-300 | Form: AEROSOL, SPRAY
Manufacturer: Fridababy, LLC
Category: otc | Type: HUMAN OTC DRUG LABEL
Date: 20250815

ACTIVE INGREDIENTS: GLYCERIN 20 mg/1 g; BENZOCAINE 20 mg/1 g
INACTIVE INGREDIENTS: HAMAMELIS VIRGINIANA ROOT BARK/STEM BARK; POTASSIUM SORBATE; ALOE BARBADENSIS LEAF JUICE; CITRIC ACID; SODIUM BENZOATE; ALCOHOL 95%; DIMETHYL ETHER; POLYETHYLENE GLYCOL 300; PPG-3 METHYL ETHER

Directions

Adults: •When practical, cleanse the affected area with mild soap and warm water, and rinse thoroughly. •Gently pat dry before use. •Hold the can upside-down and point spray nozzle 6 to 12 inches from affected area. •Apply externally up to 6 times daily or after each bowel movement.

Children under 12 years of age: consult a doctor.

Warnings

For extemal use only

FLAMMABLE. Do not use near heat,

flame, or fire or wlile smoking.

When using this product ■ Use only as
directed. ■ Do not exceed recommended
daily dosage unless directed by a doctor.
■ Intentional misuse by deliberately
concentrating or inhaling the contents
can be hmmful or fatal. ■ Do not put this
product into the rectum by using fingers
or any mechanical device or applicator.

Stop use and ask a doctor if
■ Condition worsens or does not improve
within 7 days. ■ Bleeding occurs

■ Certain persons can develop allergic

reactions to ingredients in this product. If the

symptoms being treated does not subside or if

redness, irritation, swelling, pain, or other

syptoms develop or increase, discontinue

use and consult a doctor. ■ Avoid spaying in

eyes. ■ Contents under pressure. Do not

puncture or incinerate. ■ Do not store at

temperature above 120ºF. Keep out of reach

of children. ■ If swallowed, get medical help

or contact a Poison Control Cerier right away.

Keep out of reach of children. •If swallowed, get medical help or contact a Poison Control Center right away.

Inactive Ingredients

aloe barbadensis leaf juice, citric acid, dimethyl ether, dipropylene glycol, ethanol, polyethylene glycol, potassium sorbate, PPG-3 methyl ether, sodium benzoate, witch hazel extract

Uses

■ Helps relieve discomfort

in the perianal area. ■ Temporarily protects

inflamed perianal skin.

Purpose

Local anesthetic

Protectant

PACKAGE LABEL

Upside Sown Pain Relief Spray

3.5 oz